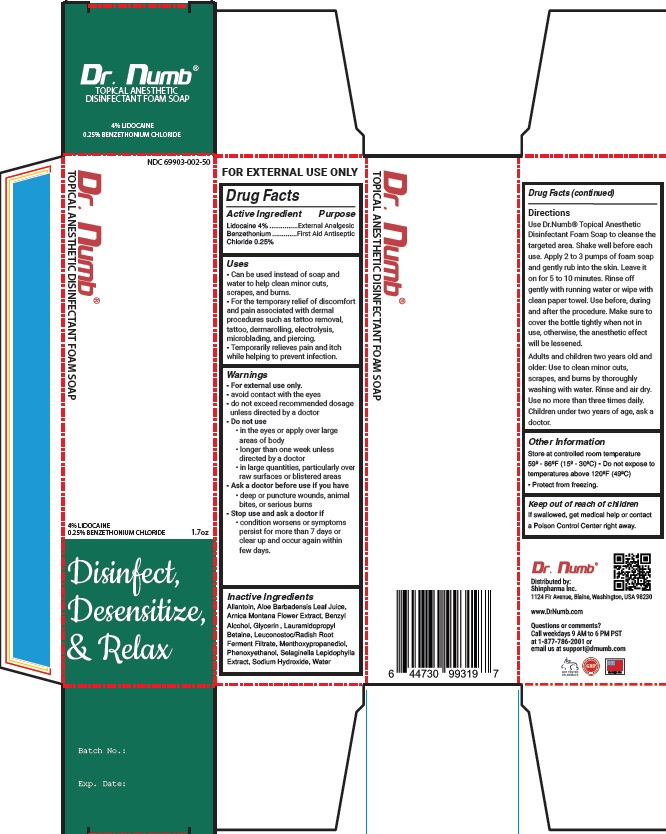 DRUG LABEL: Dr. Numb
NDC: 69903-002 | Form: CREAM
Manufacturer: Shinpharma Inc
Category: otc | Type: HUMAN OTC DRUG LABEL
Date: 20240403

ACTIVE INGREDIENTS: LIDOCAINE 4 mg/50 g; BENZETHONIUM CHLORIDE 0.25 mg/50 g
INACTIVE INGREDIENTS: ALLANTOIN; ALOE VERA LEAF; ARNICA MONTANA FLOWER; BENZYL ALCOHOL; GLYCERIN; LAURAMIDOPROPYL BETAINE; LEUCONOSTOC/RADISH ROOT FERMENT FILTRATE; 3-((L-MENTHYL)OXY)PROPANE-1,2-DIOL; PHENOXYETHANOL; SELAGINELLA LEPIDOPHYLLA; SODIUM HYDROXIDE; WATER

Drug Facts

Active Ingredient

Lidocaine 4%

benzethonium Chloride 0.25%

Purpose

External Analgesic and First Aid Antiseptic

Uses

- Can be used instead of soap and water to help clean minor cuts, scrapes, and burns
- For the temporary relief of discomfort and pain associated with dermal procedures such as tattoo removal, dermarolling, electrolysis, microblading, and piercing
- Temporarily relieves pain and itch while helping to prevent infection.

Warnings

- For external use only
- avoid contact with eyes

- do not use in large quantities particularly over raw surfaces or blistered area
- do not exceed the recommended dosage unless directed by a doctor
- in the eyes or apply over large areas of body
- longer than one week unless directed by a doctor

Ask a doctor before use if you have

- deep or puncture wounds, animal bites or serious burns

Stop the use and consult doctor if:

- condition worsenss or symptoms persist for more than 7 days or clear up and occur again within few days.

Keep out of reach of children

If swallowed, get medical help or contact a Poison Control Center right away

Directions

- Use Dr.Numb® Topical Anesthetic Foam Soap to cleanse the targeted area.
- Shake well before each use.
- Apply 2 to 3 pumps of foam soap andgently rub into the skin. Leave it onfor 5 to 10 minutes. Rinse off gentlywith running water or wipe with cleanpaper towel.
- Use before, during andafter the procedure.
- Make sure tocover the bottle tightly when not inuse, otherwise, the anesthetic effect will be lessened.

Adults and children two years old and older: Use to clean minor cuts, scrapes, and burns by thoroughly washing with water. Rinse and air dry. Use no more than three times daily.

Children under two years of age, ask a doctor.

Other information

- Store at controlled room temperature 59^0-86^0F (15^0-30^0C)
- Do not expose to temperature above 120^0F(49^0C)
- Protect from freezing

Inactive Ingredients

Allantoin, Aloe Barbadensis Leaf Juice, Arnica Montana Flower Extract, Benzyl Alcohol, Glycerin , Lauramidopropyl Betaine, Leuconostoc/Radish Root Ferment Filtrate, Menthoxypropanediol, Phenoxyethanol, Selaginella Lepidophylla Extract, Sodium Hydroxide, Water.

Question or comments?

Call weekdays 9 AM to 6 PM PST at 1-877-786-2001 or email us at support@drnumb.com

Principal Display Panel

NDC 69903-002-50

Dr.Numb

TOPICAL ANESTHETIC FOAM SOAP

4% LIDOCAINE

0.25% BENZETHONIUM CHLORIDE

DISINFECT DESENSITIZE and RELAX

1.7 oz